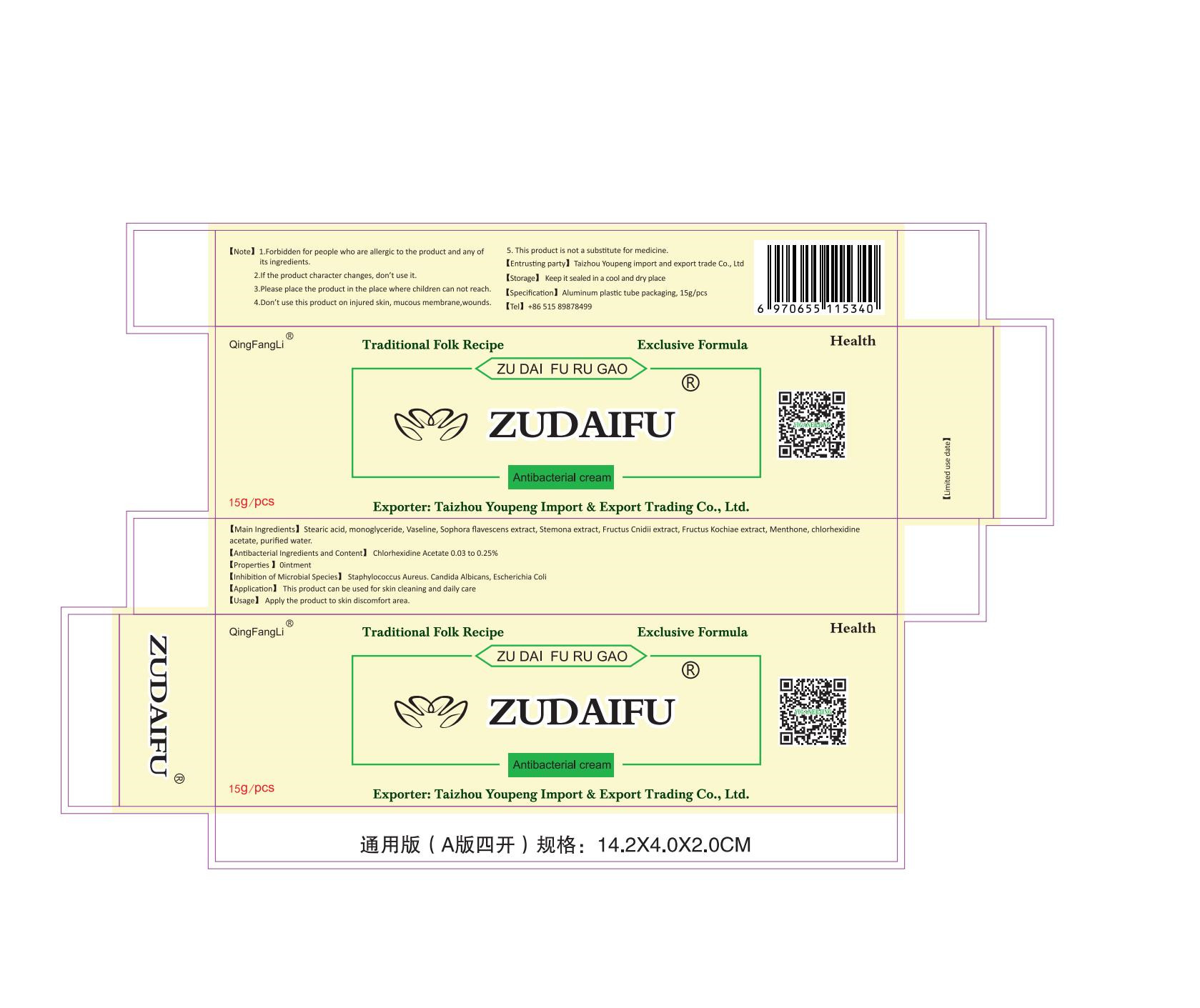 DRUG LABEL: ZUDAIFU Antibacterial Cream
NDC: 71939-004 | Form: SALVE
Manufacturer: TAIZHOU YOUPENG IMPORT AND EXPORT TRADING CO.,LTD.
Category: otc | Type: HUMAN OTC DRUG LABEL
Date: 20220310

ACTIVE INGREDIENTS: SOPHORA FLAVESCENS ROOT 75 mg/15 g; CNIDIUM MONNIERI FRUIT 30 mg/15 g; STEMONA SESSILIFOLIA ROOT 30 mg/15 g; CHLORHEXIDINE ACETATE 37.5 mg/15 g
INACTIVE INGREDIENTS: STEARIC ACID; BASSIA SCOPARIA FRUIT; MENTHONE, (+/-)-; PETROLATUM; WATER

DOSAGE AND ADMINISTRATION

Keep it sealed in a cool and dry place

INACTIVE INGREDIENT

KOCHIAEFRUCTUS,Stearic Acid,Petrolatum, Purified Water.Menthone

INDICATIONS AND USAGE

Apply the product to skin discomfort area.

ACTIVE INGREDIENT

Chlorhexldine Acetate

SOPHORAEFLAVESGEMTIS RADIX

CNIDII FRUCTUS

STEMONAE RADI

keep out of reach of children

PURPOSE

Disinfection
Sterilization
No Rinseing

WARNINGS

1.Forbidden for people who are aleric to the product and any of its ingredients.
2.if the product character changes, don't use it.
3.Please place the product in the place where children can not reach.
4.Don't use this product on injured skin, mucous membrane,wounds.
5.This product is not a substitute for medicine.